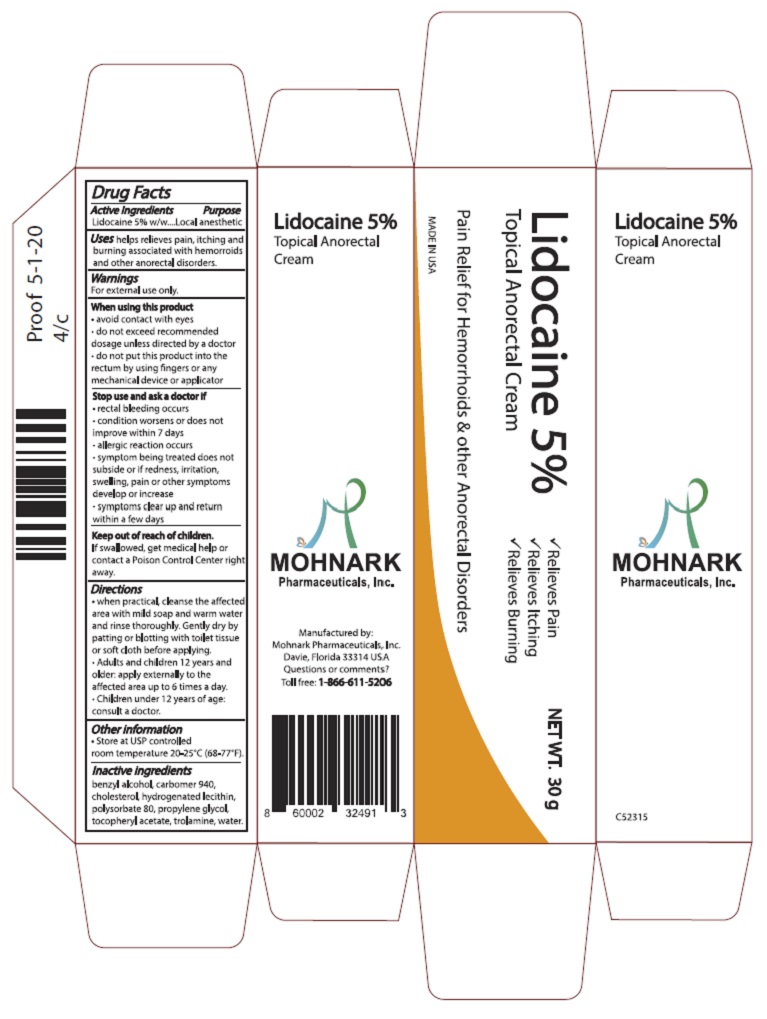 DRUG LABEL: Lidocaine 5% Topical Anorectal Cream
NDC: 73715-002 | Form: CREAM
Manufacturer: Mohnark Pharmaceuticals Inc.
Category: otc | Type: HUMAN OTC DRUG LABEL
Date: 20250513

ACTIVE INGREDIENTS: LIDOCAINE 5.25 g/100 g
INACTIVE INGREDIENTS: POLYSORBATE 80 2 g/100 g; WATER 80 g/100 g

Lidocaine 5% Topical Anorectal Cream

Active Ingredients

Lidocaine 5% w/w

Purpose

Local Anesthetic

Uses

helps relieves pain, itching and burning associated with hemorrhoids and other anorectal disorders

Warnings

For external use only

When using this product

- avoid contact with eyes
- do not exceed recommended dosage unless directed by a doctor
- do not put this product into the rectum by using fingers or any mechanical device or applicator

Stop use and ask doctor if

- rectal bleeding occurs
- condition worsens or does not improve within 7 days
- allergic reaction occurs
- symptom being treated does not subside or if redness, irritation, swelling, pain or other symptoms develop or increase
- symptoms clear up and return in a few days

Keep out of reach of children

If swallowed, get medical help or contact a Poison Control Center right away.

Directions

- when practical, cleanse the affected area with mild soap and warm water and rinse thoroughly. Gently dry by patting or blotting with toilet tissue or soft cloth before applying.
- Adults and children 12 years and older: apply externally to the affected area up to 6 times a day.
- Children under 12 years of age: consult a doctor.

Other information

- Store at USP controlled room temperature 20-25oC (68-77oF).

Inactive ingredients

benzyl alcohol, carbomer 940, cholesterol, hydrogenated lecithin, polysorbate 80, propylene glycol, tocopheryl acetate, trolamine, water.

Dosage

50 milligrams/gram per application

Usage

- Adults and children 2 years and older: apply externally to the affected area up to 3-4 times a day.
- Children under 2 years of age: consult a doctor